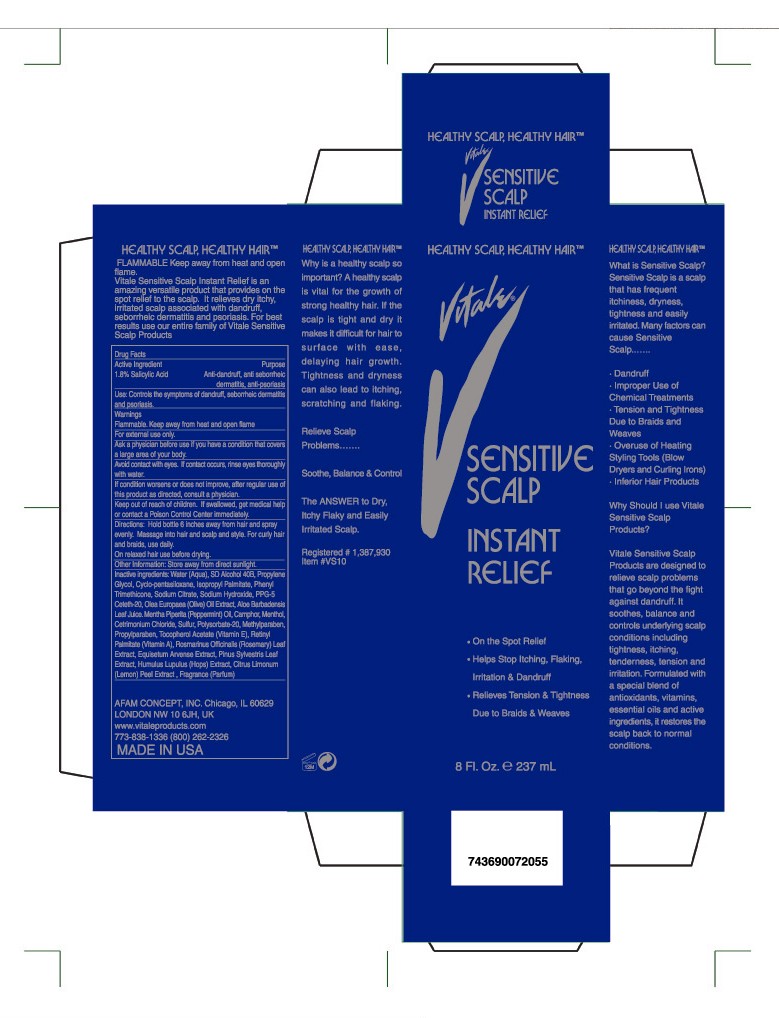 DRUG LABEL: Vitale Sensitive Scalp 12 in 1 Instant Relief Anti Dandruff Spray 
NDC: 49681-002 | Form: SPRAY
Manufacturer: JF Labs, Inc.
Category: otc | Type: HUMAN OTC DRUG LABEL
Date: 20090916

ACTIVE INGREDIENTS: Salicylic Acid 15 mg/1 mL
INACTIVE INGREDIENTS: Water; Alcohol; Propylene Glycol; Isopropyl Palmitate; Sodium Citrate; Sodium Hydroxide; Olive Oil; Aloe Vera Leaf; Peppermint Oil; Camphor; Menthol; Cetrimonium Chloride; Sulfur; Polysorbate 20; Methylparaben; Propylparaben; Alpha-tocopherol Acetate; Vitamin A Palmitate; Equisetum Arvense Extract; Cyclomethicone 5

Drug Facts

Active Ingredient | Purpose
1.8% Salicylic Acid | Anti-dandruff, anti seborrheic dermatitis, anti-psoriasis

USE

Controls the symptoms of dandruff, seborrheic dermatitis and psoriasis.

WARNINGS SECTION

Keep out of reach of children. If swallowed, get medical help or contact a Poison Control Center immediately.

Flammable. Keep away from heat and open flame.

For external use only

Ask a physician before use it you have a condition that covers a large area of your body.

Avoid contact with eyes. If contact occurs, rinse eyes thoroughly with water.

If condition worsens or does not improve, after regular use of this product as directed, consult a physician.

DOSAGE AND ADMINISTRATION SECTION

Directions: Hold bottle 6 inches away from hair and spray evenly. Massage into hair and scalp and style. For curly hair and braids, use daily. On relaxed hair use before drying.

Other Information: Store away from direct sunlight.

INACTIVE INGREDIENT SECTION

Inactive ingedients: Water(Aqua), SD Alcohol 40B, Propylene Glycol, Cyclo-pentasiloxane, Isopropyl Palmitate, Phenyl Trimethicone, Sodium Citrate, Sodium Hydroxide, PPG-5 Ceteth-20, Olea Europaea (Olive) Oil, Aloe Barbadensis Leaf Juice, Mentha Piperita (Peppermint) Oil, Camphor, Menthol, Cetrimonium Chloride, Sulfur, Polysorbate-20, Methylparaben, Propylparaben, Tocopherol Acetate (Vitamin E), Retinyl Palmitate (Vitmin A), Rosmarinus Officinalis (Rosemary) Leaf Extract, Equisetum Arvense Extract, Pinus Sylvestris Leaf Extract, Humulus Lupulus (Hops) Extract, Citrus Limonum (Lemon) Peel Extract, Fragrance (Parfum)

PACKAGE LABEL

AFAM CONCEPT, INC.
Chicago, IL 60629
LONDON NW 10 6JH, UK
www.vitaleproducts.com
(773)838-1336, (800) 262-2326
Registered # 1,387,930